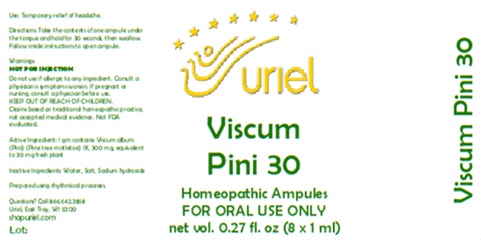 DRUG LABEL: Viscum Pini 30
NDC: 48951-9319 | Form: LIQUID
Manufacturer: Uriel Pharmacy Inc.
Category: homeopathic | Type: HUMAN OTC DRUG LABEL
Date: 20260113

ACTIVE INGREDIENTS: VISCUM ALBUM FRUITING TOP 1 [hp_X]/1 mL
INACTIVE INGREDIENTS: WATER; SODIUM CHLORIDE

Viscum Pini 30

PURPOSE

Use: Temporary relief of headache.

INDICATIONS AND USAGE

FOR ORAL USE ONLY

DOSAGE AND ADMINISTRATION

Directions: Take the contents of one ampule under the tongue and hold for 30 seconds, then swallow. Follow inside instructions to open ampule.

Warnings:
Do not use if allergic to any ingredient. Consult a physician is symptoms worsen. If pregnant or nursing, consult a physician before use.
KEEP OUT OF REACH OF CHILDREN.
Claims based on traditional homeopathic practice, not accepted medical evidence. Not FDA evaluated.

KEEP OUT OF REACH OF CHILDREN.

Active Ingredient: 1 gm contains: Viscum album - Pini (Pine tree mistletoe) 1X, 300 mg, equivalent to 30 mg fresh plant

Inactive Ingredients: Water, Salt, Sodium Hydroxide

Prepared using rhythmical processes.

Questions? Call 866.642.2858
Uriel, East Troy, WI 53120
shopuriel.com Lot: